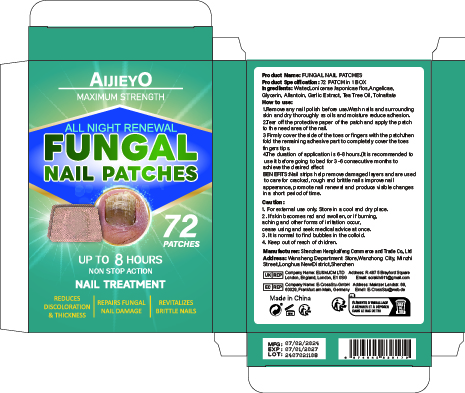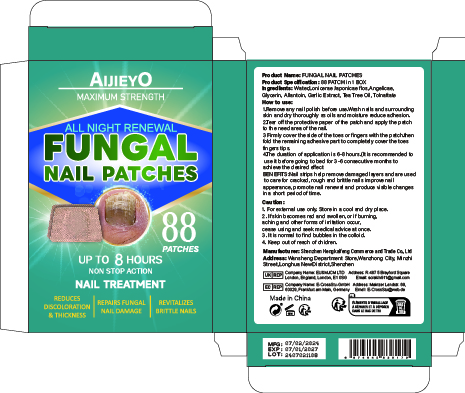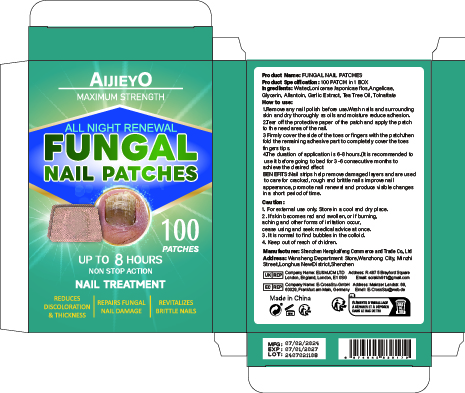 DRUG LABEL: Nail Renew Patches
NDC: 84117-025 | Form: PATCH
Manufacturer: Shenzhen Hengkaifeng Commerce and Trade Co., Ltd
Category: otc | Type: HUMAN OTC DRUG LABEL
Date: 20240905

ACTIVE INGREDIENTS: TOLNAFTATE 1 g/100 1
INACTIVE INGREDIENTS: ANGELICA SINENSIS ROOT; GARLIC; LONICERA JAPONICA FLOWER; WATER; ALLANTOIN; TEA TREE OIL; GLYCERIN

Active ingredients

Tolnaftate ≤1%

PURPOSE

Anti-fungal

Uses

Uses for relief and treatment of pain,soreness, and inflammation from nail fungus.
Symptoms: ■ discolored nails ■ brittle nails ■ distorted nails

Warnings

For external use only, Some individuals may be sensitive to essential oils.
Begin with a small drop to determine if product causes any irritation. Discontinue use if any irritation occurs.
Stop use and consult a doctor if condition worsens, Not for use on children under the age of 2 without physician direction.

Stop use and ask a doctor if

rash occur

Do not use

on damaged or broken skik

When using this product

Directions shake well before use.
Wash and thoroughly dry the affected area.
Apply 1-2 drops and gently rub into affected area three times per day.
Wash hands after applying

Keep out of reach of children.

If swallwed, get medical help or contact a Poison Control Center right away.

inactive ingredients

Water

Lonicerae Japonicae flos

Angelicae

Glycerin

Allantoin

Garlic Extract

Tea Tree Oil

DOSAGE & ADMINISTRATION

shake well before use.Wash and thoroughly dry the affectedarea. Apply 1-2 drops and gently rubinto affected area three times per day.